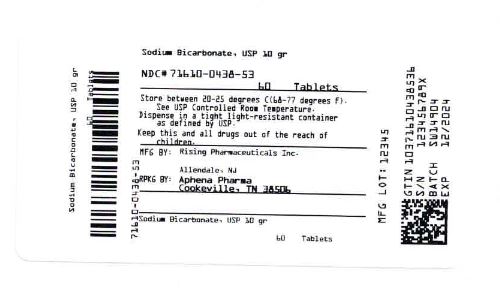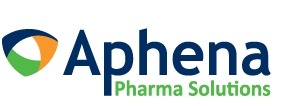 DRUG LABEL: Sodium Bicarbonate
NDC: 71610-438 | Form: TABLET
Manufacturer: Aphena Pharma Solutions - Tennessee, LLC
Category: otc | Type: Human OTC Drug Label
Date: 20200706

ACTIVE INGREDIENTS: SODIUM BICARBONATE 650 mg/1 1
INACTIVE INGREDIENTS: CROSCARMELLOSE SODIUM; CELLULOSE, MICROCRYSTALLINE; SILICON DIOXIDE; STEARIC ACID; TALC

Sodium Bicarbonate 10 gr Tablets, USP
Antacid

DO NOT USE IF IMPRINTED SAFETY SEAL UNDER CAP IS BROKEN OR MISSING

Drug Facts
Active ingredients (in each tablet)
Sodium Bicarbonate 10 gr (650mg)

Purpose
Antacid

INDICATIONS AND USAGE

Uses: relieves • acid indigestion • heartburn • sour stomach • upset stomach associated with these symptoms

Warnings
Do not take more than 24 tablets for adults up to 60 years of age (or 12 tablets for adults 60 years of age and older) in a 24-hour period nor use the maximum dosage for more than 2 weeks, except under the advice and supervision of a physician.
Ask a doctor before use if you have a sodium restricted diet.
Ask a doctor or pharmacist before use if you are taking a prescription drug.
Antacids may interact with certain prescription drugs.
Stop use and ask a doctor if symptoms last more than 2 weeks
If pregnant or breast-feeding, ask a health professional before use.

Keep out of reach of children.
In case of accidental overdose, seek professional assistance or contact a Poison Control Center immediately.

Directions

- do not use the maximum dosage for more than 2 weeks
- tablets may be swallowed whole or dissolved in water prior to use
- adults 60 years of age and over: 1-2 tablets every 4 hours, not more than 12 tablets in 24 hours
- adults under 60 years of age: 1-4 tablets every 4 hours, not more than 24 tablets in 24 hours

Other Information: Each tablet contains: sodium 178 mg (7.74 mEq) • store at room temperature 15°-30°C (59°-86°F) in a well closed container as defined in the USP.

INACTIVE INGREDIENT

Inactive Ingredients: Croscarmellose sodium NF, microcrystalline cellulose NF, silica NF, stearic acid NF and talc USP.

Questions? 1-866-562-4597

11790-11-16 REV 11/16

Manufactured for: Manufactured by:
Rising Pharmaceuticals, Inc. Contract Pharmacal Corp.
Allendale, NJ 07401 Hauppauge, NY 11788

Lot No.:

Exp. Date:

Repackaging Information

Please reference the How Supplied section listed above for a description of individual tablets. This drug product has been received by Aphena Pharma - TN in a manufacturer or distributor packaged configuration and repackaged in full compliance with all applicable cGMP regulations. The package configurations available from Aphena are listed below:

Count | 10 gr
60 | 71610-438-53
90 | 71610-438-60
120 | 71610-438-70
180 | 71610-438-80
360 | 71610-438-94

Store between 20°-25°C (68°-77°F). See USP Controlled Room Temperature. Dispense in a tight light-resistant container as defined by USP. Keep this and all drugs out of the reach of children.

Repackaged by:
Cookeville, TN 38506
20200706JH

PRINCIPAL DISPLAY PANEL - 10 gr

NDC 71610-438 - Sodium Bicarbonate 10 gr Tablets